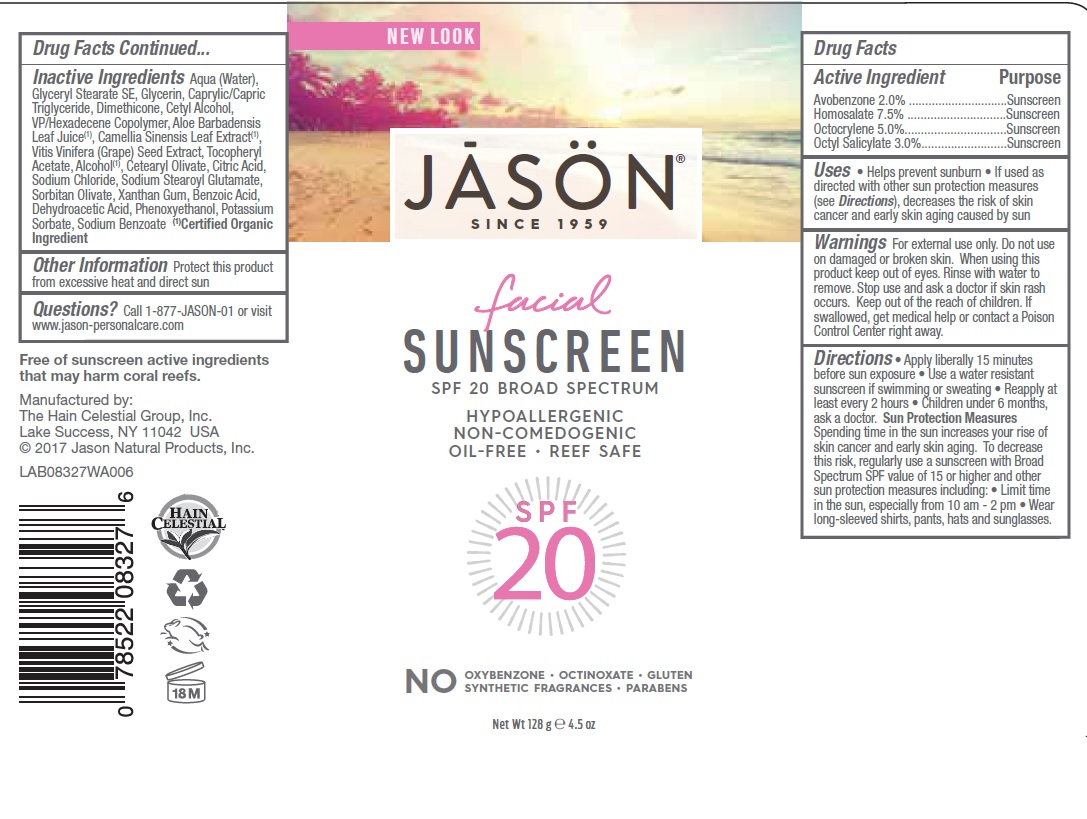 DRUG LABEL: J0832706 Jason Sun Facial Sunscreen SPF20
NDC: 61995-0027 | Form: LOTION
Manufacturer: The Hain Celestial Group, Inc.
Category: otc | Type: HUMAN OTC DRUG LABEL
Date: 20210412

ACTIVE INGREDIENTS: AVOBENZONE 2 g/100 g; HOMOSALATE 7.5 g/100 g; OCTISALATE 3 g/100 g; OCTOCRYLENE 5 g/100 g
INACTIVE INGREDIENTS: ALCOHOL; VINYLPYRROLIDONE/HEXADECENE COPOLYMER; SODIUM STEAROYL GLUTAMATE; .ALPHA.-TOCOPHEROL ACETATE; GLYCERYL STEARATE SE; POTASSIUM SORBATE; CETYL ALCOHOL; DIMETHICONE; XANTHAN GUM; MEDIUM-CHAIN TRIGLYCERIDES; CETEARYL OLIVATE; SODIUM CHLORIDE; SORBITAN OLIVATE; SODIUM BENZOATE; CITRIC ACID MONOHYDRATE; ALOE VERA LEAF; GLYCERIN; WATER; GREEN TEA LEAF; VITIS VINIFERA SEED; BENZOIC ACID; DEHYDROACETIC ACID; PHENOXYETHANOL

J0832706 Jason Sun Facial Sunscreen SPF20

Active Ingredient

Avobenzone - 2.0%

Homosalate - 7.5%

Octocrylene -5.0%

Octyl Salicylate - 3.0%

DOSAGE AND ADMINISTRATION

Apply liberally 15 minutes before sun exposure.Use a water resistant sunscreenif swimming or sweating. Reapply at least every 2 hours. Children under 6 months, ask a doctor

PURPOSE

Sunscreen

WARNINGS

For external use only. Do not use on damaged or broken skin. When using this product keep out of eyes. Rinse with water to remove. Stop use and ask a doctor if skin rash occurs.

Keep out of reach of children. If swallowed get medical help or contact Poison Center right away.

INACTIVE INGREDIENT

Water, Glyceryl Stearate SE, Glycerin, Caprylic/Capric Triglyceride, Dimethicone, Cetyl Alcohol, VP/Hexadecene Copolymer, Aloe Barbadensis Leaf Juice(1), Camellia Sinensis Leaf Extract (1), Vitis Venifera (Grape) Seed Extract (1), Tocopheryl Acetate, Alcohol (1), Cetearyl Olivate, Citric Acid, Sodium Chloride, Sodium Stearoyl Glutamate, Sorbitan Olivate, Xanthan Gum, Benzoic Acid, Dehydroacetic Acid, Phenoxyethanol, Potassium Sorbate, Sodium Benzoate.

(1) Certified Organic Ingredient

INDICATIONS AND USAGE

Helps prevents sunburns. If used as directed with other sun protection measures, decreases risk of skin cancer and early skin aging caused by sun exposure. Skin Protection Measures: Spending time in the sun increases your risk of skin cancer and early skin aging. To decrease risk, regularly use sunscreen with Broad Spectrum SPF 15 or higher and other protective measures including: limit time in sun, especially from10am to 2pm, and wear long sleeved shirts, pants, hats and sunglases.